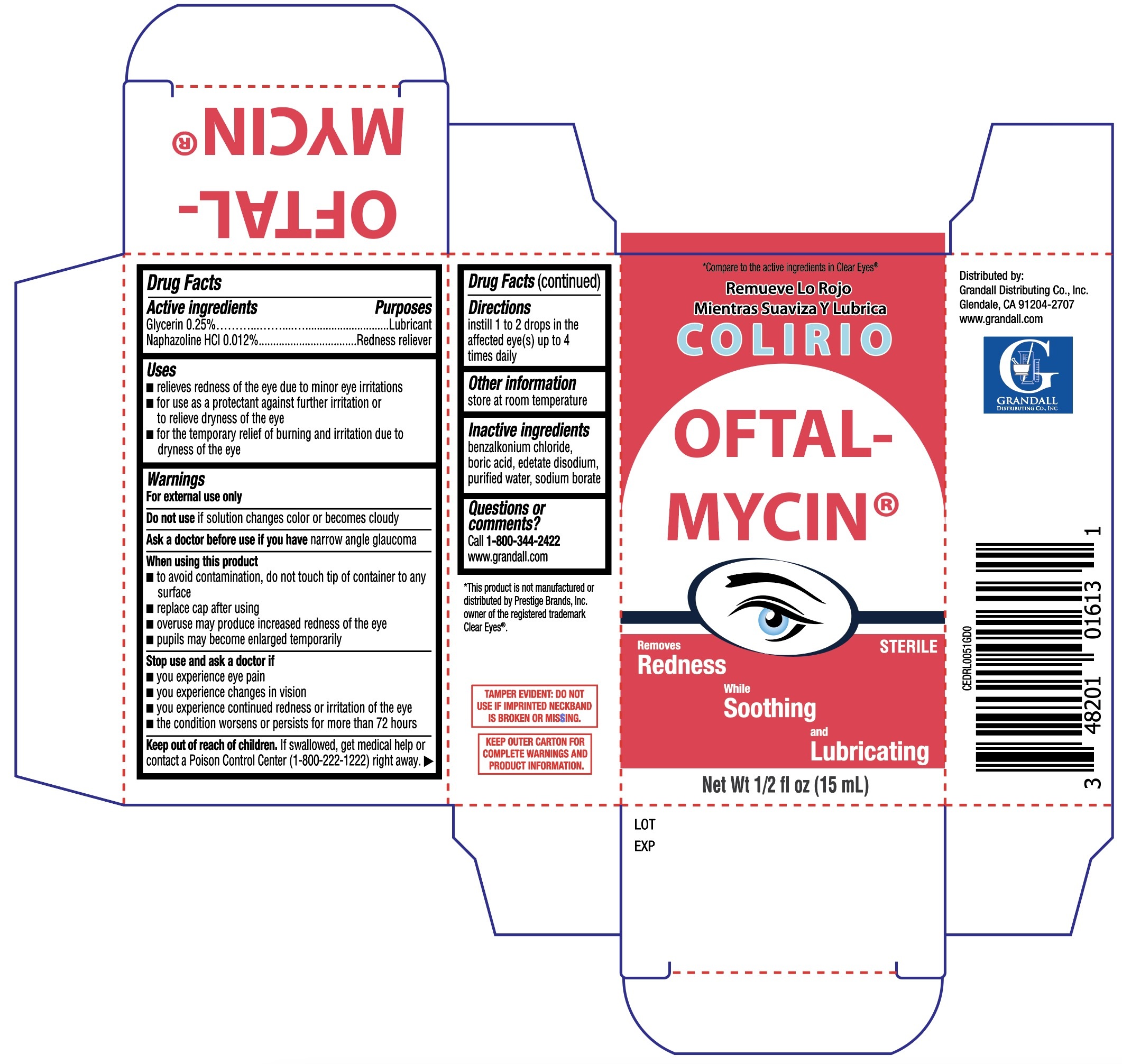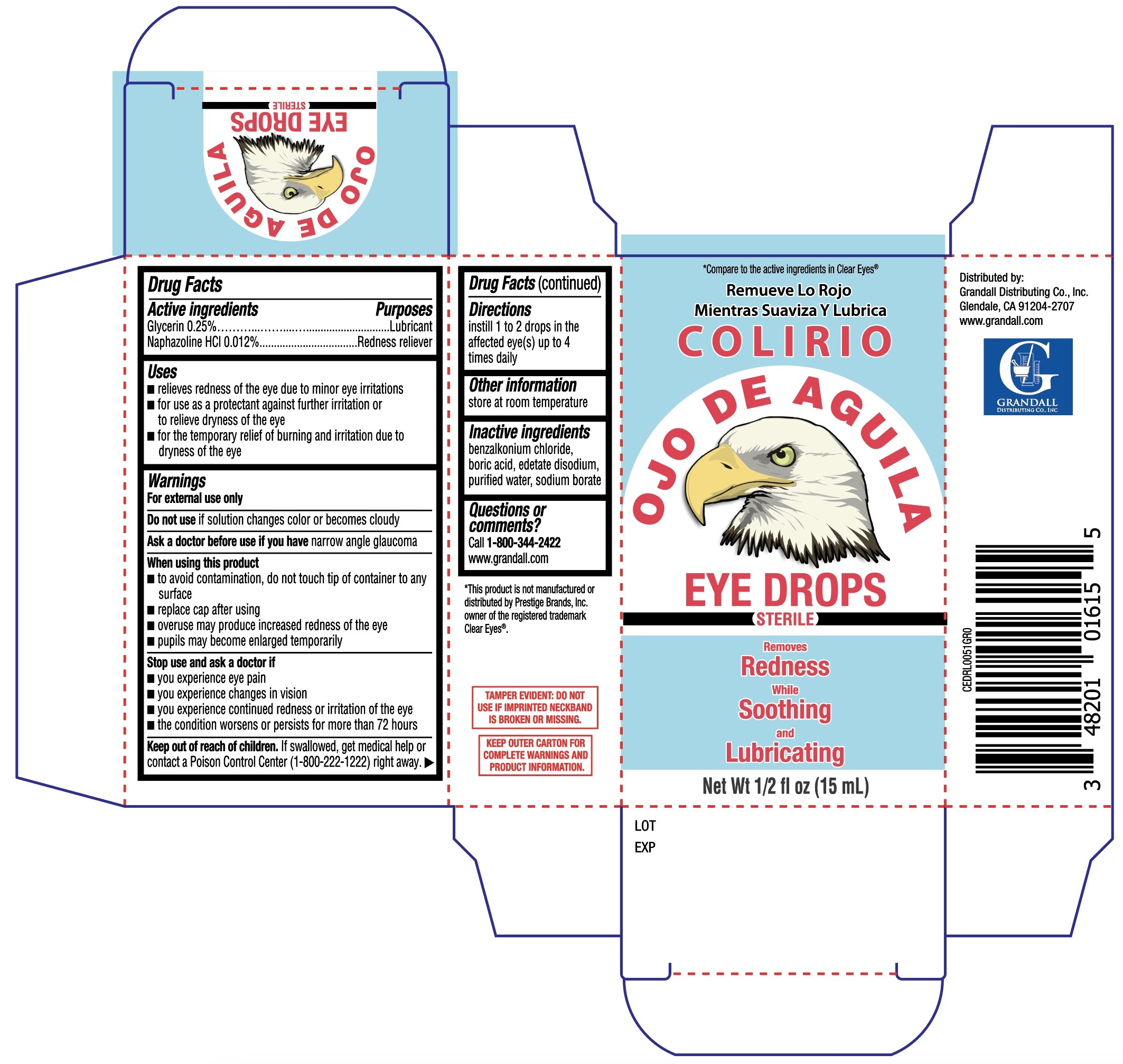 DRUG LABEL: Colirio Ojo De Aguila Eye Drops
NDC: 48201-106 | Form: SOLUTION/ DROPS
Manufacturer: Grandall Distributing Co., Inc.
Category: otc | Type: HUMAN OTC DRUG LABEL
Date: 20251231

ACTIVE INGREDIENTS: GLYCERIN 0.25 g/100 mL; NAPHAZOLINE HYDROCHLORIDE 0.012 g/100 mL
INACTIVE INGREDIENTS: WATER; SODIUM BORATE; BORIC ACID; EDETATE DISODIUM; BENZALKONIUM CHLORIDE

Colirio Ojo De Aguila Eye Drops15mL (PLD)
Colirio Oftal-Mycin 15mL (PLD)

Active Ingredients

Glycerin 0.25%

Naphazoline hydrochloride 0.012%

Purpose

Lubricant and redness reliever

Uses

- relieves redness of the eye due to minor eye irritations
- for use as a protectant against further irritation or to relieve dryness of the eye
- temporarily relieves burning and irritation due to dryness of the eye

Warnings

For external use only

Do not use this product if

- solution changes color or becomes cloudy

Ask a doctor before use

if you have narrow angle glaucoma

When using this product

- do not touch tip of container to any surface to avoid contamination
- replace cap after using
- overuse may cause more redness of the eye
- pupils may become enlarged temporarily

Stop use and ask a doctor if

- you feel eye pain
- changes in vision occur
- redness or irritation of the eye lasts
- condition worsens
- symptoms last for more than 72 hours

Keep out of reach of children.

If swallowed, get medical help or contact a Poison Control Center (1800-222-1222) right away.

Directions

Instill 1 or 2 drops in the affected eye(s) up to 4 times daily

Other information

store at room temperature

Inactive ingredients

benzalkonium chloride, boric acid, edetate disodium, purified water, sodium borate

Questions or Comments?

Call 1-800-344-2422

www.grandall.com